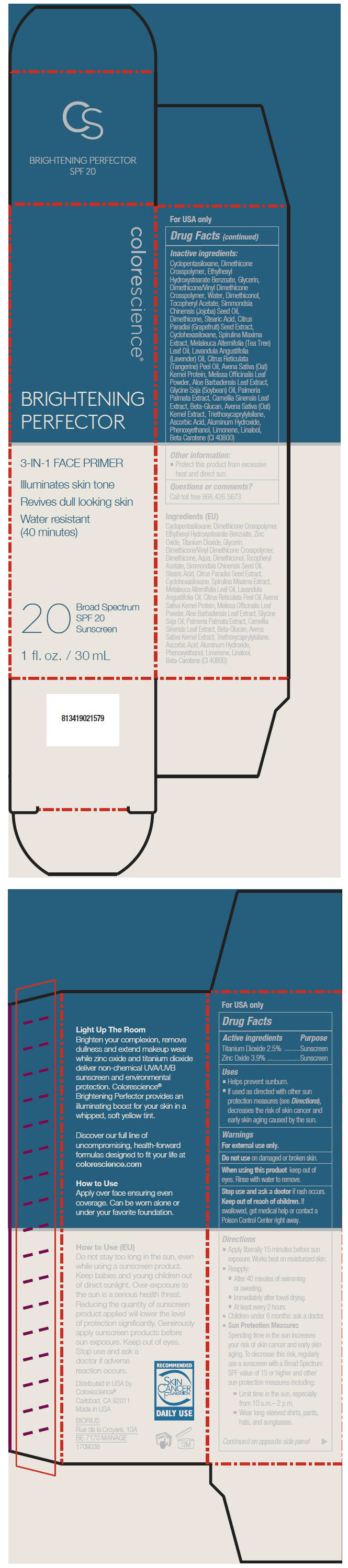 DRUG LABEL: Brightening Perfector SPF 20 Sunscreen
NDC: 68078-015 | Form: LIQUID
Manufacturer: Colorescience
Category: otc | Type: HUMAN OTC DRUG LABEL
Date: 20181106

ACTIVE INGREDIENTS: Titanium Dioxide 25 mg/1 mL; Zinc Oxide 39 mg/1 mL
INACTIVE INGREDIENTS: Cyclomethicone 5; DIMETHICONE CROSSPOLYMER (450000 MPA.S AT 12% IN CYCLOPENTASILOXANE); Ethylhexyl Hydroxystearate Benzoate; Glycerin; DIMETHICONE/VINYL DIMETHICONE CROSSPOLYMER (SOFT PARTICLE); Water; DIMETHICONOL (100000 CST); .Alpha.-Tocopherol Acetate; JOJOBA OIL; Dimethicone; Stearic Acid; CITRUS PARADISI SEED; Cyclomethicone 6; ARTHROSPIRA MAXIMA; TEA TREE OIL; LAVENDER OIL; CITRUS RETICULATA LEAF OIL; OAT; MELISSA OFFICINALIS LEAF; ALOE VERA LEAF; SOYBEAN OIL; DULSE; GREEN TEA LEAF; POLYSACCHARIDE-K; Triethoxycaprylylsilane; Ascorbic Acid; Aluminum Hydroxide; Phenoxyethanol; Limonene, (+)-; .BETA.-CAROTENE; LINALOOL, (+/-)-

Brightening Perfector SPF 20 Sunscreen

Drug Facts

ACTIVE INGREDIENT

Active ingredients | Purpose
Titanium Dioxide 2.5% | Sunscreen
Zinc Oxide 3.9% | Sunscreen

Uses

- Helps prevent sunburn.
- If used as directed with other sun protection measures (see Directions), decreases the risk of skin cancer and early skin aging caused by the sun.

Warnings

For external use only.

Do not use on damaged or broken skin.

When using this product keep out of eyes. Rinse with water to remove.

Stop use and ask a doctor if rash occurs.

Keep out of reach of children. If swallowed, get medical help or contact a Poison Control Center right away.

Directions

- Apply liberally 15 minutes before sun exposure. Works best on moisturized skin.
- Reapply:
  - After 40 minutes of swimming or sweating.
  - Immediately after towel drying.
  - At least every 2 hours.
- Children under 6 months: ask a doctor.
- Sun Protection Measures
  Spending time in the sun increases your risk of skin cancer and early skin aging. To decrease this risk, regularly use a sunscreen with a Broad Spectrum SPF value of 15 or higher and other sun protection measures including:
  - Limit time in the sun, especially from 10 a.m.– 2 p.m.
  - Wear long-sleeved shirts, pants, hats, and sunglasses.

Inactive ingredients

Cyclopentasiloxane, Dimethicone Crosspolymer, Ethylhexyl Hydroxystearate Benzoate, Glycerin, Dimethicone/Vinyl Dimethicone Crosspolymer, Water, Dimethiconol, Tocopheryl Acetate, Simmondsia Chinensis (Jojoba) Seed Oil, Dimethicone, Stearic Acid, Citrus Paradisi (Grapefruit) Seed Extract, Cyclohexasiloxane, Spirulina Maxima Extract, Melaleuca Alternifolia (Tea Tree) Leaf Oil, Lavandula Angustifolia (Lavender) Oil, Citrus Reticulata (Tangerine) Peel Oil, Avena Sativa (Oat) Kernel Protein, Melissa Officinalis Leaf Powder, Aloe Barbadensis Leaf Extract, Glycine Soja (Soybean) Oil, Palmeria Palmata Extract, Camellia Sinensis Leaf Extract, Beta-Glucan, Avena Sativa (Oat) Kernel Extract, Triethoxycaprylylsilane, Ascorbic Acid, Aluminum Hydroxide, Phenoxyethanol, Limonene, Linalool, Beta Carotene (CI 40800)

Other information

- Protect this product from excessive heat and direct sun.

Questions or comments?

Call toll free 866.426.5673

Distributed in USA by
Colorescience®
Carlsbad, CA 92011

PRINCIPAL DISPLAY PANEL - 30 mL Tube Carton

colorescience®

BRIGHTENING
PERFECTOR

3-IN-1 FACE PRIMER

Illuminates skin tone

Revives dull looking skin

Water resistant
(40 minutes)

20
Broad Spectrum
SPF 20
Sunscreen

1 fl. oz. / 30 mL